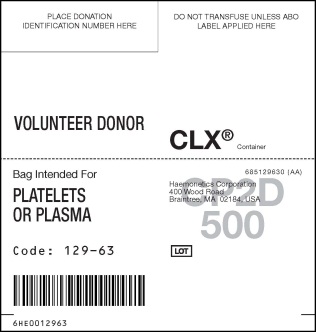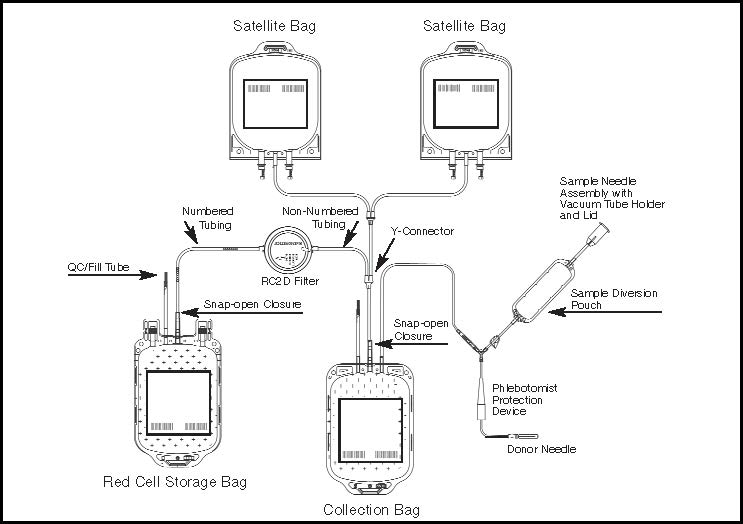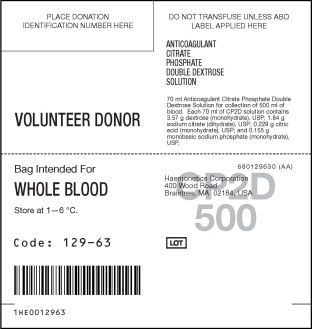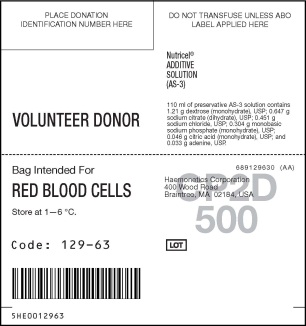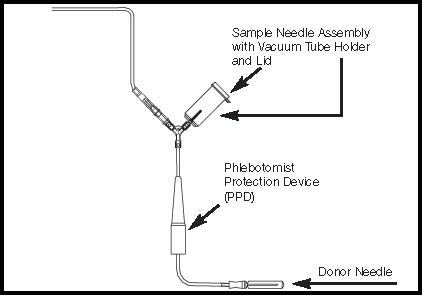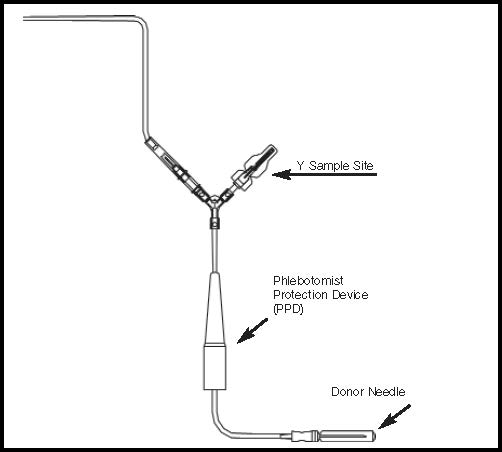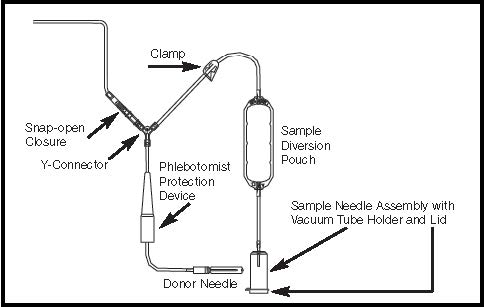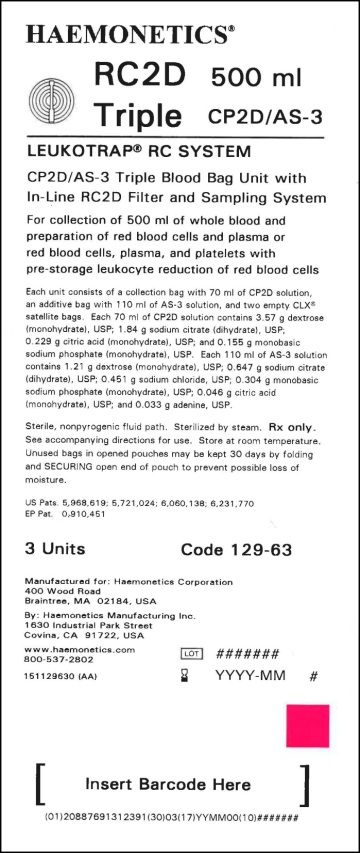 DRUG LABEL: Leukotrap
NDC: 53157-129 | Form: KIT | Route: INTRAVENOUS
Manufacturer: Haemonetics Manufacturing Inc
Category: prescription | Type: HUMAN PRESCRIPTION DRUG LABEL
Date: 20140929
DEA Schedule: CII

ACTIVE INGREDIENTS: DEXTROSE 3.57 g/70 mL; ADENINE 0.033 g/110 mL; DEXTROSE 1.21 g/110 mL

LEUKOTRAP® RC SYSTEM DESCRIPTION

The Leukotrap® RC System CP2D/AS-3 Blood Bag Unit with In-Line RC2D Filter and Sampling System is intended for the collection of whole blood and preparation of red blood cells and plasma or red blood cells, plasma, and platelets with pre-storage leukocyte reduction of red blood cells. The fluid pathway is sterile and non-pyrogenic. Steam Sterilized. RX only.

INDICATIONS AND USAGE

Instructions for Use for Systems Containing a Y Sampling Site (YSS) with or without a pre-attached Vacuum Tube Holder or Sample Diversion Pouch (SDP) with a pre-attached Vacuum Tube Holder. See unit foil envelope for specific product code/description being used.

Figure 1- Diagram of the Complete Product Set

I. BLOOD COLLECTION INSTRUCTIONS FORSYSTEMS CONTAINING A Y SAMPLING SITE (YSS) ONLY

Figure 2- Donor Line with Y Sampling Site Only

ACCOMPLISHING PHLEBOTOMY

1. Load blood collection mixer or suspend blood bag on donor scale. Adjust to desired collection volume or weight as per operating instructions for whichever equipment is being used. Place collection bag on blood collection mixer or donor scale as far below donor arm as possible.
2. If not previously performed, place a temporary clamp on the donor tubing between the donor needle and Y-connector.
3. Disinfect site of phlebotomy and apply pressure to donor arm. If using a blood pressure cuff, inflate to not more than 60 mm Hg. If desired, secure the tubing to the donor’s arm with tape below Phlebotomist Protection Device (PPD). Note:Steps 1 through 3 can be performed in any order.
4. Remove donor needle cover by first twisting the cover at the base to break the seal, and then remove cover carefully.
5. Perform phlebotomy. Remove the temporary clamp, if used, and ensure there is blood flow.
6. Stabilize the donor needle with tape.
7. If not previously performed, further stabilize the donor needle by taping the tubing below the PPD.
8. Reduce pressure on donor’s arm as needed.

COLLECTING BLOOD

1. Collect appropriate volume of blood into collection bag, as indicated on packaging. Notes: If blood collection mixer is used, follow manufacturer's operating instructions. Mix blood and anticoagulant frequently during collection; for example, once every 45 seconds and immediately after collection.
2. After required amount of blood has been collected, seal donor tubing between the Y Sampling Site and the collection bag.* Note: If pre-filtration quality control (QC) is to be performed, use the QC tubing attached to the collection bag. If additional tubing is needed, leave the desired amount of tubing containing anticoagulated blood attached to the collection bag.

COLLECTING SAMPLES FROM Y SAMPLING SITE

Note: When using YSS systems with a pre-attached vacuum tube holder, go to Section II.

1. For blood sampling, remove the Y Sampling Site needle cover. Ensure the protective sheath is in place over the sampling needle.
2. Fasten a vacuum tube holder onto the base of the sampling needle and collect samples.

Precautions:During sample collection ensure the vacuum tubes are centered within the vacuum tube holder and maintain forward pressure on the vacuum tube. Note:After the last tube is collected, it is recommended that the vacuum tube holder be left in place.

DISCONTINUING PHLEBOTOMY

1. After blood samples are collected, release any remaining pressure from donor’s arm.
2. Remove the tape stabilizing the donor needle and tubing. Advance PPD over the donor needle hub.
3. If desired, clamp tubing behind the PPD. Note: Steps 1 through 3 can be performed in any order.
4. While holding the top of the PPD, grasp the tubing below the PPD and pull the donor needle into the PPD with a continuous motion until the needle is completely withdrawn and secured into place.
5. If desired, insert the PPD into the vacuum tube holder.
6. Detach and discard the donor/needle assembly (e.g. needle, PPD, sample diversion pouch, and tubing) in the usual manner.*
7. Strip the tubing between seal and collection bag, gently mix the whole blood and allow the tubing to refill OR seal off the tubing, detach and discard in the usual manner.

Continue to "Centrifugation", Section IV, Step 1.

II. BLOOD COLLECTION INSTRUCTIONS FORSYSTEMS CONTAINING A Y SAMPLING SITE (YSS) WITH A PRE-ATTACHED VACUUM TUBE HOLDER

Figure 3- Donor Line with Y Sampling Site and Pre-attached Vacuum Tube Holder with Lid

ACCOMPLISHING PHLEBOTOMY

1. Load blood collection mixer or suspend blood bag on donor scale. Adjust to desired collection volume or weight as per operating instructions for whichever equipment is being used. Place collection bag on blood collection mixer or donor scale as far below donor arm as possible.
2. If not previously performed,place a temporary clamp on the donor tubing between thedonor needle and Y-connector.
3. Disinfect site of phlebotomy and apply pressure to donor arm. If using a blood pressure cuff, inflate to not more than 60 mm Hg. If desired, secure the tubing to the donor’s arm with tape below Phlebotomist Protection Device (PPD). Note:Steps 1 through 3 can be performed in any order.
4. Remove donor needle cover by first twisting the cover at the base to break the seal, and then remove cover carefully.
5. Perform phlebotomy. Remove the temporary clamp, if used, and ensure there is blood flow.
6. Stabilize the donor needle with tape.
7. If not previously performed, further stabilize the donor needle by taping the tubing below the PPD.
8. Reduce pressure on donor’s arm as needed.

COLLECTING BLOOD

1. Collect appropriate volume of blood into collection bag, as indicated on packaging. Notes: If blood collection mixer is used, follow manufacturer's operating instructions. Mix blood and anticoagulant frequently during collection; for example, once every 45 seconds and immediately after collection.
2. After required amount of blood has been collected, seal donor tubing between the Y Sampling Site and the collection bag.* Note: If pre-filtration quality control (QC) is to be performed, use the QC tubing attached to the collection bag. If additional tubing is needed, leave the desired amount of tubing containing anticoagulated blood attached to the collection bag.

COLLECTING SAMPLES FROM Y SAMPLING SITE SYSTEMS WITH A PRE-ATTACHED VACUUM TUBE HOLDER

1. Open lid of the vacuum tube holder and collect samples. Precautions: During sample collection ensure the vacuum tubes are centered within the vacuum tube holder and maintain forward pressure on the vacuum tube.
2. After the final sample collection, close the lid on the vacuum tube holder.

DISCONTINUING PHLEBOTOMY

1. After blood samples are collected, release any remaining pressure from donor’s arm.
2. Remove the tape stabilizing the donor needle and tubing. Advance PPD over the donor needle hub.
3. If desired, clamp tubing behind the PPD. Note: Steps 1 through 3 can be performed in any order.
4. While holding the top of the PPD, grasp the tubing below the PPD and pull the donor needle into the PPD with a continuous motion until the needle is completely withdrawn and secured into place.
5. If desired, insert the PPD into the vacuum tube holder.
6. Detach and discard the donor/needle assembly (e.g. needle, PPD, sample diversion pouch, and tubing) in the usual manner.*
7. Strip the tubing between seal and collection bag, gently mix the whole blood and allow the tubing to refill OR seal off the tubing, detach and discard in the usual manner.
8. Continue to "Centrifugation", Section IV, Step 1.

III. BLOOD COLLECTION INSTRUCTIONS FOR SYSTEMS CONTAINING A SAMPLE DIVERSION POUCH WITH A PRE-ATTACHED VACUUM TUBE HOLDER

Figure 4- Donor Line with Sample Diversion Pouch with a Pre-attached Vacuum Tube Holder

ACCOMPLISHING PHLEBOTOMY:

1. Load blood collection mixer or suspend blood bag on donor scale. Adjust to desired collection volume or weight as per operating instructions for whichever equipment is being used. Place collection bag on blood collection mixer or donor scale as far below donor arm as possible.
1. If not previously performed, place a temporary clamp on the donor tubing between the donor needle and Y-connector, if required.
2. Disinfect site of phlebotomy and apply pressure to donor arm. If using a blood pressure cuff, inflate to not more than 60 mm Hg. If desired, secure the tubing to the donor’s arm with tape below Phlebotomist Protection Device (PPD). Note: Steps 1 through 3 can be performed in any order.
3. Remove donor needle cover by first twisting the cover at the base to break the seal, and then remove cover carefully.
4. Perform phlebotomy. Remove the temporary clamp, if used, and ensure there is blood flow. The donor’s blood will automatically flow into the sample diversion pouch.
5. Stabilize the donor needle with tape. Warning: To avoid risk of air embolism to donor, do not squeeze sample diversion pouch while tubing to the pouch is open. Ensure sample diversion pouch remains below the donor arm while tubing to the pouch is open. Note: Do not reduce pressure on donor’s arm until the snap-open closure has been opened (see Step 10).
6. If not previously performed, further stabilize the donor needle by taping the tubing below the PPD.
7. Once the sample diversion pouch is filled with the desired amount of blood, close clamp immediately on tubing between the sample diversion pouch and Y connector.
8. Seal tubing between the sample diversion pouch and Y connector to maintain sterility of the system prior to sample collection.*
9. Open snap-open closure on the Y connector to initiate blood flow into the collection bag. Reduce pressure on donor’s arm as needed.

COLLECTING SAMPLES FROM SAMPLE DIVERSION POUCH:

1. Position the sample diversion pouch so that the air rises to the top of the pouch (away from the vacuum tube holder).
2. Open lid of the vacuum tube holder and collect samples. Precautions: During sample collection ensure the vacuum tubes are centered within the vacuum tube holder and maintain forward pressure on the vacuum tube. Collect blood samples from the sample diversion pouch into vacuum tube(s) within approximately four minutes to avoid possible clot formation. Drawing air into a vacuum tube may cause hemolysis.
3. After the final sample collection, close the lid on the vacuum tube holder.

COLLECTING BLOOD:

1. Collect appropriate volume of blood into collection bag as indicated on packaging. Notes: If blood collection mixer is used, follow manufacturer's operating instructions. Mix blood and anticoagulant frequently during collection; for example, once every 45 seconds and immediately after collection.

DISCONTINUING PHLEBOTOMY:

1. After required amount of blood has been collected, seal donor tubing between snap-open closure and collection bag.*
2. Note: If pre-filtration quality control (QC) is to be performed, use the QC tubing attached to the collection bag. If additional tubing is needed, leave the desired amount of tubing containing anticoagulated blood attached to the collection bag.
3. Release any remaining pressure from donor’s arm.
4. Remove the tape stabilizing the donor needle and tubing. Advance PPD over the donor needle hub.
5. If desired, clamp tubing behind the PPD.
  Note: Steps 1 through 4 can be performed in any order.
  While holding the top of the PPD, grasp the tubing below the PPD and pull the donor needle into the PPD with a continuous motion until the needle is completely withdrawn and secured into place.
6. While holding the top of the PPD, grasp the tubing below the PPD and pull the donor needle into the PPD with a continuous motion until the needle is completely withdrawn and secured into place.
7. If desired, insert the PPD into the vacuum tube holder.
8. Detach and discard the donor/needle assembly (e.g. needle, PPD, sample diversion pouch, and tubing) in the usual manner.*
9. Strip the tubing between seal and collection bag, gently mix the whole blood and allow the tubing to refill OR seal off the tubing, detach and discard in the usual manner.

IV. BLOOD PROCESSING INSTRUCTIONS:CENTRIFUGATION

1. Load unit into centrifuge bucket, ensuring that the tubing stays in the top half of the bucket. When bags and tubing are positioned in the bucket, place the red blood cell filter in a horizontal position on top of the entire assembly and secure with tape, band, or Leukotrap® Strap.
2. Centrifuge at appropriate conditions to produce desired components.

V. BLOOD PROCESSING INSTRUCTIONS: PREPARING SET

Note:Prior to expression, ensure tubing between the Y-connector and the filter (non-numbered tubing) is clamped. For efficient processing, the tubing may be clamped prior to removing the unit from the centrifuge bucket.

1. Carefully remove the unit from the centrifuge and place the bag containing red cells in the plasma expressor.
2. Gently apply expressor pressure.
3. If not previously clamped, clamp the non-numbered tubing between the Y-connector and the filter.
4. Clamp tubing to extra satellite bag, if present.

VI. BLOOD PROCESSING INSTRUCTIONS: EXPRESSING PLASMA

1. Open snap-open closure of the bag containing red cells and express plasma or platelet-rich plasma into a satellite bag.
2. Stop expression by clamping or sealing the tubing leading to satellite bag(s) and release expressor pressure.
3. If not already sealed, seal tubing below the Y-connector leading to all satellite bags.* Detach and set aside the plasma or platelet-rich plasma for further processing.

Notes: If preparing a platelet concentrate, the platelet-rich plasma should be separated from the red blood cells within 8 hours after collection. If preparing Fresh Frozen Plasma, the plasma should be separated from the red blood cells and placed in the freezer at –18 °C or colder within 8 hours after blood collection. If preparing Plasma Frozen within 24 Hours after Phlebotomy, the plasma should be separated from the red blood cells and placed in the freezer at –18 °C or colder within 24 hours after blood collection.

VII. BLOOD PROCESSING INSTRUCTIONS: TRANSFERRING ADDITIVE

Note:The snap-open closure may be opened prior to hanging the bag containing the AS-3 additive solution for additive transfer, provided the non-numbered tubing between the bag containing the red cells and the filter is clamped.

1. Hang the bag containing the AS-3 additive solution so that the numbered tubing is fully extended and ensure the filter is in a vertical position and above the bag.
2. Open clamp or snap-open closure of the bag containing the AS-3 additive solution, and transfer to the bag containing red blood cells. Note: AS-3 additive solution should be added to the bag containing the red blood cells immediately after plasma or platelet-rich plasma removal.
3. Transfer AS-3 additive solution under one of the following conditions:
A. Within 8 hours of collection if blood is held at room temperature.
B. Within 72 hours of collection if blood is refrigerated after collection.

VIII. BLOOD FILTRATION INSTRUCTIONS

1. Clamp the non-numbered tubing prior to raising the bag containing red blood cells and AS-3 additive solution for mixing in order to avoid the introduction of air into the filter.
2. Mix red cells gently and thoroughly.
3. Hang the collection bag at one of the following heights:
A. 60 ± 2 inches for blood stored and filtered at room temperature.
B. 60 to 72 inches for blood stored and filtered at 1—6 °C.
4. Ensure filter is vertical and remove clamp to allow red blood cells to gravity flow through the filter and into the red cell storage bag. Notes: Do not apply mechanical or manual pressure to increase flow rate. Filtration can begin at room temperature up to 8 hours or at 1—6 °C up to 72 hours post-collection. If unit has not completely filtered by 8 hours post-collection at room temperature, filtration must be completed at 1—6 °C. Filtration at maximum head height may shorten filtration times. “Head height” is the distance from the top of the bag containing the blood to be filtered to the horizontal plane where the filtered blood bag rests. Filtration can be unattended. Filtration times can be influenced by collection and processing conditions and biological variability of donors. Experimental data with some filter products indicate that a prolonged filtration can be an indication of sub-optimal leukocyte reduction.
5. Filtration is complete when the collection bag is empty. To maximize red blood cell recovery, allow the tubing above the filter to empty.
6. Clamp and seal tubing below the filter.* The numbered tubing downstream of the filter will not drain. Notes: If the numbered tubing below the filter has drained (emptied) after filtration, it is recommended to perform a residual white blood cell count on the unit. Do not strip tubing prior to sealing the tubing below the filter. If it is desired to strip blood from numbered tubing, do so only after tubing has been sealed close to the filter and detached. If it is necessary to strip blood from numbered tubing, care should be taken when stripping is performed. Increased (mechanical) hemolysis has been associated with stripping when blood is cold and has a higher hematocrit. Do not strip forcefully or frequently against a snap-open closure.
7. Detach and discard collection bag and filter.*
8. If desired, seal at or adjacent to "X" marks on tubing to provide numbered segments of anticoagulated blood for typing or crossmatching.* If quality control is to be performed on post-filtration sample, use the attached QC line on the bag containing red cells.
9. Store CP2D/AS-3 preserved red blood cells at 1—6 °C for up to 42 days and use as indicated. Note: If AS-3 additive solution is not used, whole blood or red blood cells in CP2D alone may be stored at 1—6 °C for up to 21 days.

IX. QUALITY CONTROL TESTING

Percent red cell recovery should be determined by following FDA Guidance entitled “ Guidance for Industry - Pre-Storage Leukocyte Reduction of Whole Blood and Blood Components Intended for Transfusion”, published in September 2012.
During processing, always observe the following precautions:

1. Sealing should be done in a manner that avoids fluid splatter.
2. Always dispose of blood-contaminated products in a manner consistent with established BIOHAZARD safety procedures.

WARNINGS

Failure to achieve and maintain a closed system during processing will result in a product that must be transfused within 24 hours.

PRECAUTIONS

General

1. Use aseptic technique.
2. Use only if solutions are clear.
3. If moisture is observed on the outside of the collection system when removed from the cellophane pouch, subsequent handling and storage of an unused set within the foil pouch could encourage the growth of mold on the base label. Unused bags in opened foil pouches may be kept 30 days by folding and SECURING open end of pouch to prevent possible loss of moisture.

ADVERSE REACTIONS

There are no known potential adverse reactions associated specifically with theLeukotrap® RC System CP2D/AS-3 Blood Bag Unit with In-Line RC2D Filter and Sampling System.

DOSAGE AND ADMINISTRATION

1. Filter and process whole blood within 72 hours of collection.
2. When whole blood is at room temperature, filter within 8 hours of collection.
3. When whole blood is at 1 – 6 °C, filter within 72 hours of collection.
4. Follow AABB recommended guidelines for heavy spin centrifugation for component preparation. For optimal red blood cell (RBC) quality do not exceed 5000g.
5. This product is not made with natural rubber latex.
6. Tubing Specifications:
  a. OD = 0.163”
  b. ID = 0.114”
  c. Wall = 0.0245”
7. Fill line only:
  d. OD = 0.160”
  e. ID = 0.114”
  f. Wall = 0.0245”

HOW SUPPLIED

Each unit consists of:

1. Collection Bag with 70ml of CP2D solution.
2. Additive Bag with 110 ml of AS-3 solution.
3. Two empty CLX® Satellite Bags

PACKAGE/LABEL PRINCIPAL DISPLAY PANEL

Figure 5 - Envelope Label

Figure 6 - Collection Bag Label

Figure 7 - Additive/Storage Bag Label

Figure 8 – Platelet/Plasma CLX Bag Label

REFERENCES

Haemonetics®, Haemonetics The Blood Management Company® and Leukotrap® are trademarks or registered trademarks of Haemonetics Corporation in the US, other countries or both.

Manufactured for:

Haemonetics Corporation

400 Wood Road

Braintree, MA 02184, USA

By: Haemonetics Manufacturing Inc.

1630 Industrial Park Street

Covina, CA 91722, USA

www.haemonetics.com

800-537-2802

IFU P/N 147129621 (AA)